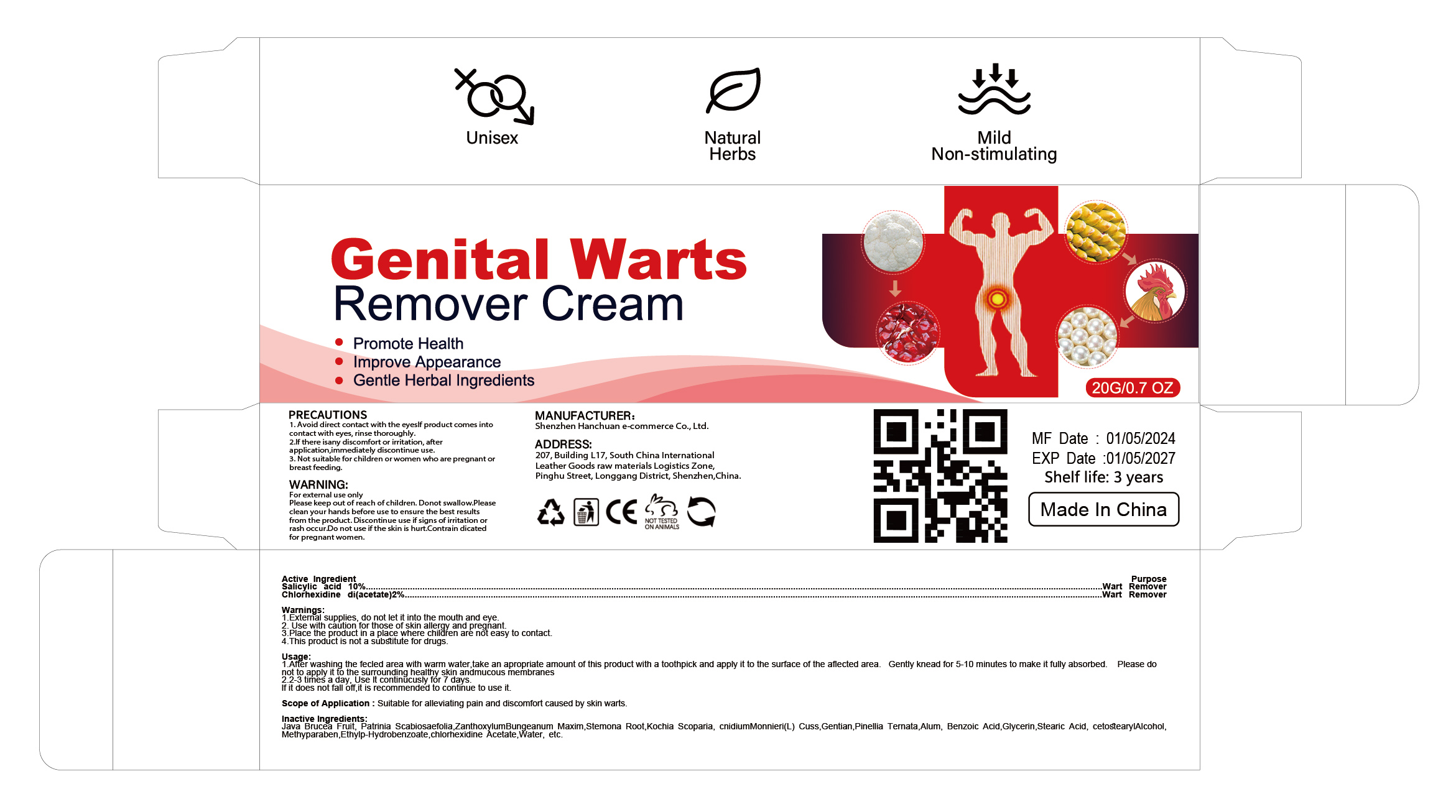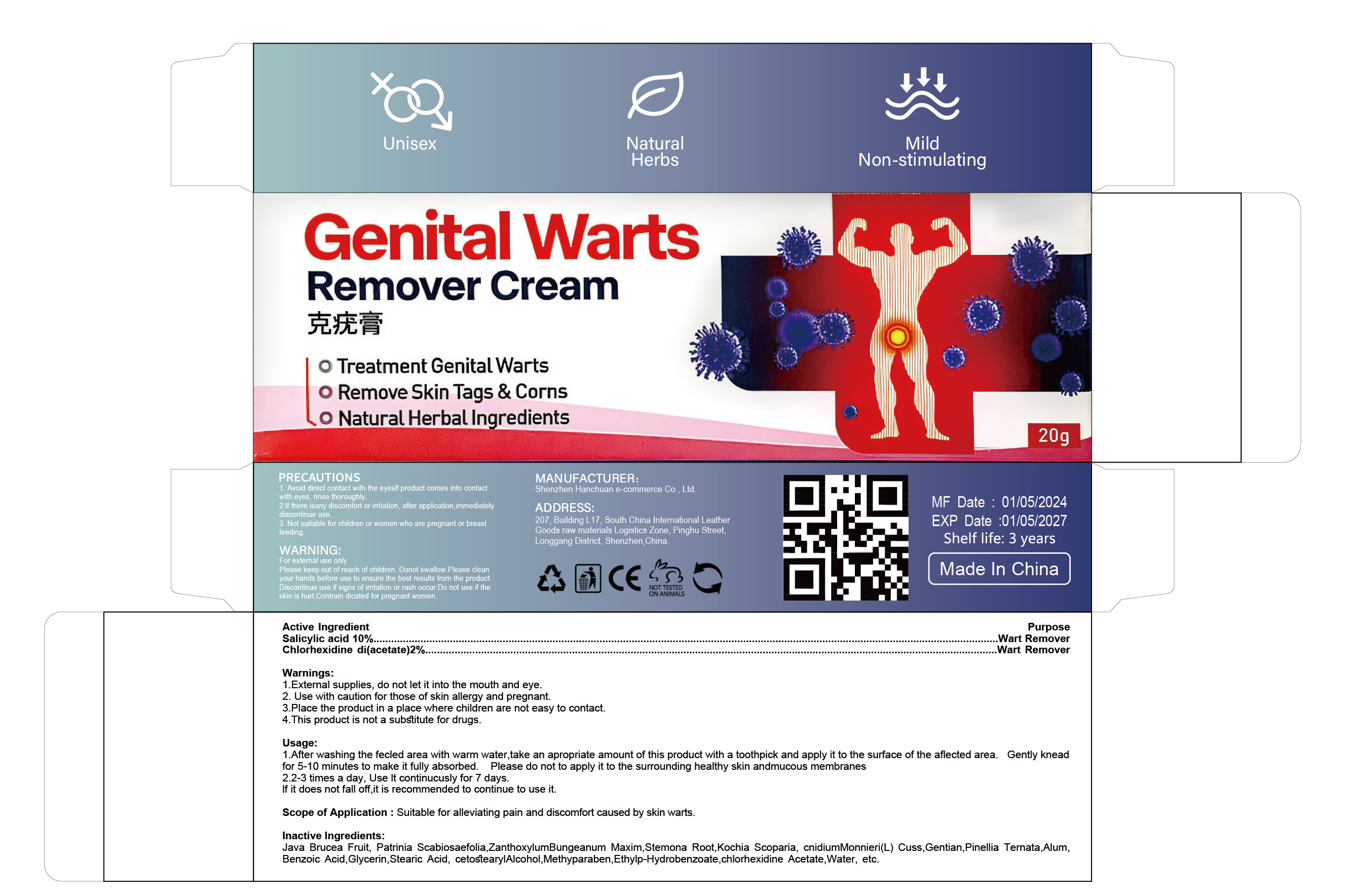 DRUG LABEL: Genital Warts Remover cream
NDC: 84302-008 | Form: OINTMENT
Manufacturer: Shenzhen Hanchuan e-commerce Co., Ltd
Category: otc | Type: HUMAN OTC DRUG LABEL
Date: 20240517

ACTIVE INGREDIENTS: SALICYLIC ACID 10 g/100 g; ACETATE ION 2 g/100 g
INACTIVE INGREDIENTS: BASSIA SCOPARIA WHOLE; PINELLIA TERNATA WHOLE; CHLORHEXIDINE ACETATE; BRUCEA JAVANICA FRUIT; CETOSTEARYL ALCOHOL; WATER; PATRINIA SCABIOSIFOLIA; ZANTHOXYLUM BUNGEANUM WHOLE; GLYCERIN; STEARIC ACID; GENTIANA LUTEA ROOT; STEMONA SESSILIFOLIA ROOT; POTASSIUM ALUM; METHYLPARABEN; ETHYLPARABEN; CNIDIUM MONNIERI WHOLE; BENZOIC ACID

Genital Warts Remover cream

ACTIVE INGREDIENT

Salicylic acid 10%

Chlorhexidine di(acetate) 2%

PURPOSE

Wart Remover

Please keep out of reach of children.

INDICATIONS AND USAGE

Suitable for alleviating pain and discomfort caused by skin warts

WARNINGS

1.External supplies, do not let it into the mouth and eye.
2. Use with caution for those of skin allergy and pregnant.
3.Place the product in a place where children are not easy to contact
4.This product is not a substitute for drugs

DOSAGE AND ADMINISTRATION

After washing the fecled area with warm water,take an apropriate amount of this product with a toothpick and apply it to the surface of the aflected area. Gently knead for 5-10 minutes to make it fully absorbed. Please do not to apply it to the surrounding healthy skin andmucous membranes
2.2-3 times a day, Use it continucusly for 7 days.
If it does not fall off,it is recommended to continue to use it

INACTIVE INGREDIENT

Java Brucea Fruit
Patrinia Scabiosaefolia
ZanthoxylumBungeanum Maxim
Stemona Root
Kochia Scoparia
cnidiumMonnieri(L) Cuss
Gentian
Pinellia Ternata
Alum
Benzoic Acid
Glycerin
Stearic Acid
cetostearylAlcohol
Methyparaben
Ethylp-Hydrobenzoate
chlorhexidine Acetate
Water